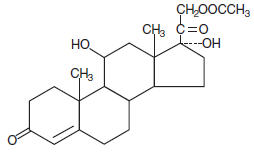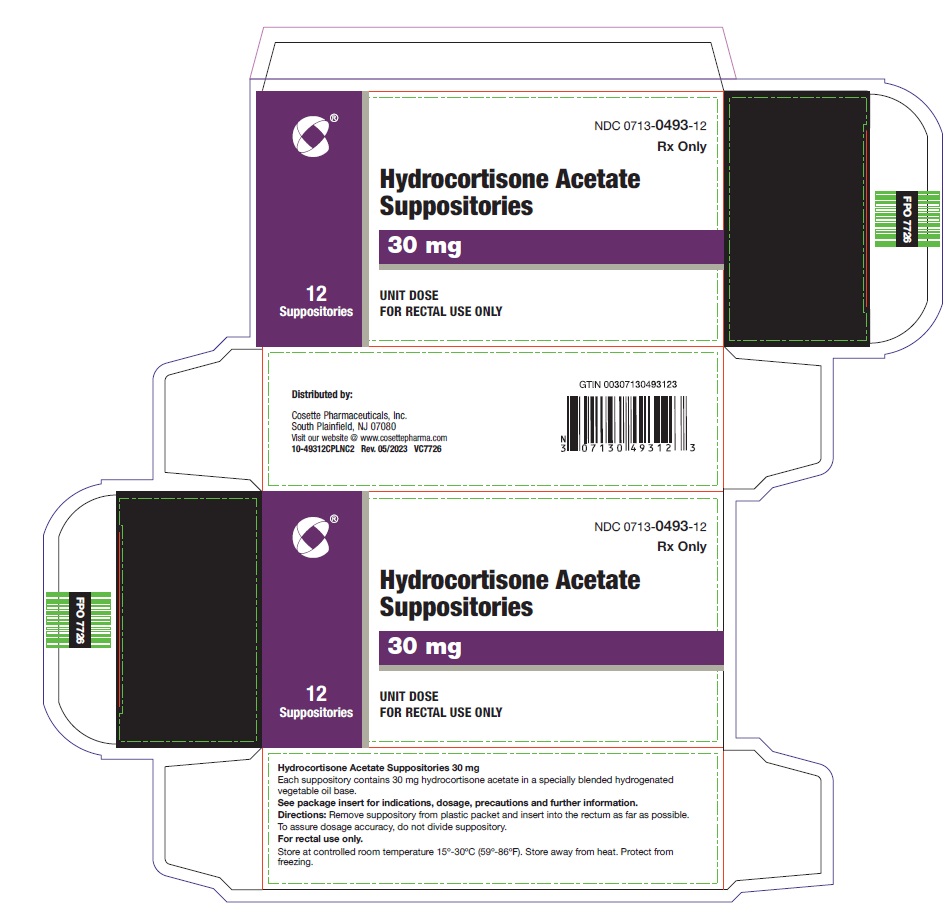 DRUG LABEL: Hydrocortisone Acetate
NDC: 0713-0493 | Form: SUPPOSITORY
Manufacturer: Cosette Pharmaceuticals, Inc.
Category: prescription | Type: HUMAN PRESCRIPTION DRUG LABEL
Date: 20231123

ACTIVE INGREDIENTS: HYDROCORTISONE ACETATE 30 mg/1 1
INACTIVE INGREDIENTS: HYDROGENATED PALM KERNEL OIL

HYDROCORTISONE ACETATE, 30 mg
Rectal Suppositories
Rx only

DESCRIPTION

Each Hydrocortisone Acetate Suppository for rectal administration contains 30 mg hydrocortisone acetate, USP in a specially blended hydrogenated vegetable oil base.

Hydrocortisone acetate is a corticosteroid. The molecular weight of hydrocortisone acetate is 404.50. Chemically, hydrocortisone acetate is pregn-4-ene-3, 20 dione, 21-(acetyloxy)-11, 17-dihydroxy-, (11β)- with an empirical formula of C23H32O6 and the following structural formula:

CLINICAL PHARMACOLOGY

In normal subjects, about 26 percent of hydrocortisone acetate is absorbed when the hydrocortisone acetate suppository is applied to the rectum. Absorption of hydrocortisone acetate may vary across abraded or inflamed surfaces.

Topical steroids are primarily effective because of their anti-inflammatory, antipruritic and vasoconstrictive action.

INDICATIONS AND USAGE

Hydrocortisone Acetate Suppositories are indicated for use in inflamed hemorrhoids, post irradiation (factitial) proctitis, as an adjunct in the treatment of chronic ulcerative colitis, cryptitis, other inflammatory conditions of the anorectum, and pruritus ani.

CONTRAINDICATIONS

Hydrocortisone Acetate Suppositories are contraindicated in those patients with a history of hypersensitivity to any of the components.

PRECAUTIONS

Do not use unless adequate proctologic examination is made.

If irritation develops, the product should be discontinued and appropriate therapy instituted.

In the presence of an infection, the use of an appropriate antifungal or antibacterial agent should be instituted. If a favorable response does not occur promptly, Hydrocortisone Acetate Suppositories should be discontinued until the infection has been adequately controlled.

Carcinogenesis

No long-term studies in animals have been performed to evaluate the carcinogenic potential of corticosteroid suppositories.

Pregnancy Category C and Nursing Mothers

In laboratory animals, topical steroids have been associated with an increase in the incidence of fetal abnormalities when gestating females have been exposed to rather low dosage levels. There are no adequate and well-controlled studies in pregnant women.

It is not known whether this drug is excreted in human milk. Since many drugs are excreted in human milk and because of the potential for serious adverse reactions in nursing infants from Hydrocortisone Acetate Suppositories, a decision should be made whether to discontinue nursing or to discontinue taking the drug, taking into account the importance of the drug to the mother.

Until adequate studies in pregnant or lactating women have been conducted, this drug should be used during pregnancy or by nursing mothers only when clearly needed and when the potential benefits outweigh the potential risks to the fetus. Drugs of this class should not be used extensively on pregnant patients, in large amounts, or for prolonged periods of time.

ADVERSE REACTIONS

The following local adverse reactions have been reported with Hydrocortisone Acetate Suppositories:

1. Burning 5. Folliculitis

2. Itching 6. Hypopigmentation

3. Irritation 7. Allergic Contact Dermatitis

4. Dryness 8. Secondary Infection

To report SUSPECTED ADVERSE REACTIONS, contact Cosette Pharmaceuticals, Inc. at 1-800-922-1038 or FDA at 1-800-FDA-1088 or www.fda.gov/medwatch.

Drug abuse and dependence have not been reported in patients treated with Hydrocortisone Acetate Suppositories.

OVERDOSAGE

If signs and symptoms of systemic overdosage occur, discontinue use.

DOSAGE AND ADMINISTRATION

Usual dosage: One suppository in the rectum twice daily morning and night for two weeks, in nonspecific proctitis. In more severe cases, one suppository three times daily; or two suppositories twice daily. In factitial proctitis, recommended therapy is six to eight weeks or less, according to response.

HOW SUPPLIED

Hydrocortisone Acetate Suppositories are easy to open and available in cartons of:

12's NDC 0713-0493-12

STORAGE AND HANDLING

Store at controlled room temperature 15° to 30° C (59° to 86° F). Store away from heat. Protect from freezing.

Distributed by:
Cosette Pharmaceuticals, Inc.
South Plainfield, NJ 07080

8-0493CPLNC1
Iss. 01/2021 VC7545

PRINCIPAL DISPLAY PANEL - 30 mg Carton

NDC 0713- 0493-12

Rx Only

Hydrocortisone Acetate Suppositories

30 mg

UNIT DOSE

12 Suppositories

FOR RECTAL USE ONLY

Cosette Pharmaceuticals, Inc.